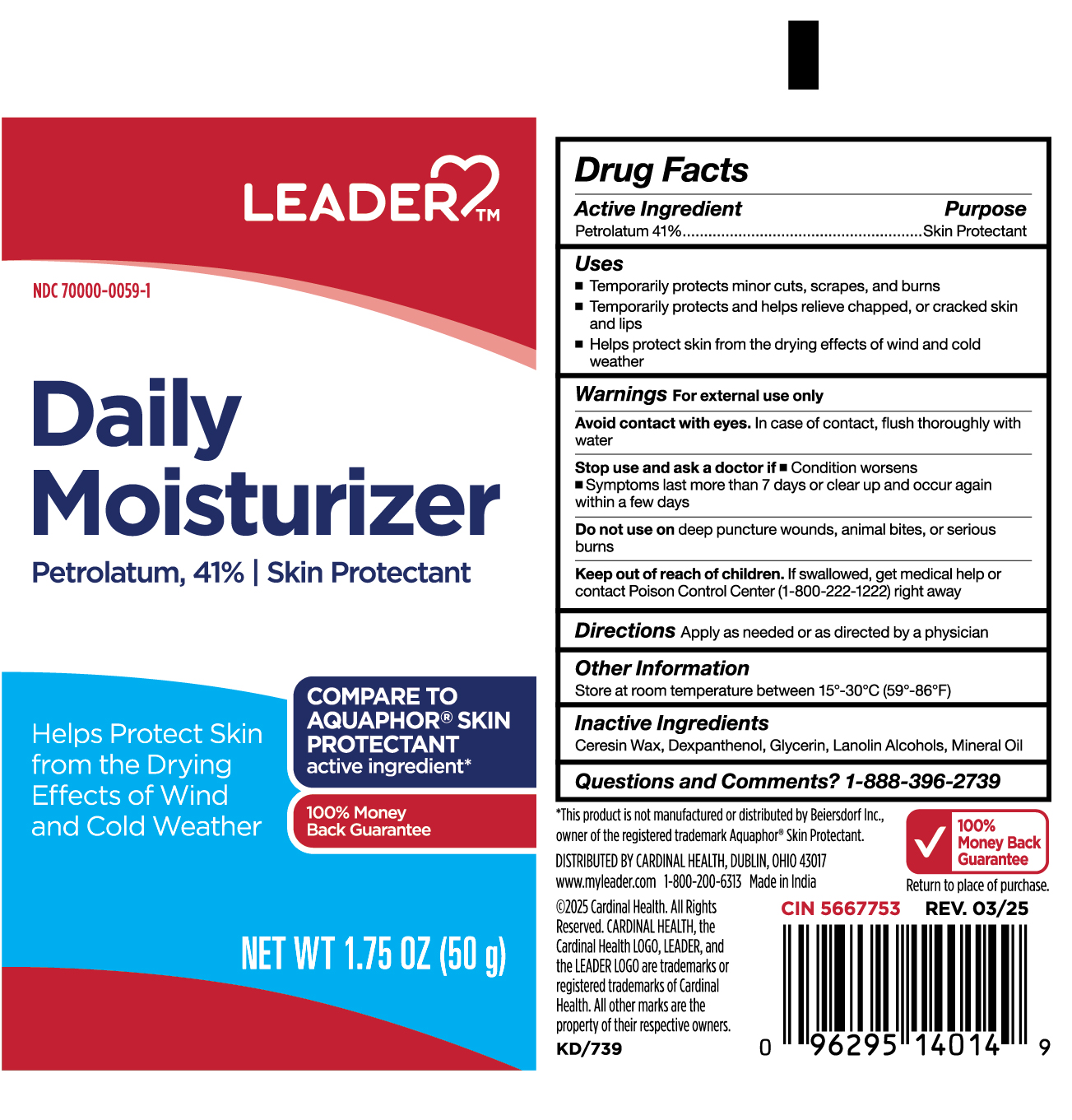 DRUG LABEL: CR-5667753 Leader Daily Moisturizer
NDC: 70000-0059 | Form: OINTMENT
Manufacturer: Cardinal Health
Category: otc | Type: HUMAN OTC DRUG LABEL
Date: 20250404

ACTIVE INGREDIENTS: PETROLATUM 41 g/100 g
INACTIVE INGREDIENTS: LANOLIN ALCOHOLS; MINERAL OIL; DEXPANTHENOL; GLYCERIN; CERESIN

CR-5667753 Leader Daily Moisturizer

Active Ingredient

Petrolatum 41%

Purpose

Skin Protectant

Uses

- Temporarily protects minor cuts, scrapes, and burns
- Temporarily protects and helps relieve chapped, or cracked skin and lips
- Helps protect skin from the drying effects of wind and cold weather

Warnings

For external use only

Avoid contact with eyes.

In case of contact, flush thoroughtly with water

Stop Use and ask a doctor if

- Condition worsens
- Symptoms last more than 7 days or clear up and occur again within a few days

Do not use on

Deep puncture wounds, animal bites, or serious burns

Keep out of reach of children.

If swallowed, get medical help or contact a Poison Control Center (1-800-222-1222) right away

Directions

Apply as needed or as directed by a physician

Other Information

Store at room temperature between 15º-30ºC (59º-86ºF)

Inactive Ingredients

Ceresin Wax, Dexpanthenol, Glycerin, Lanolin Alcohols, Mineral Oil

Questions and Comments?

1-888-396-2739

Label

CR-5667753 Daily Moisture